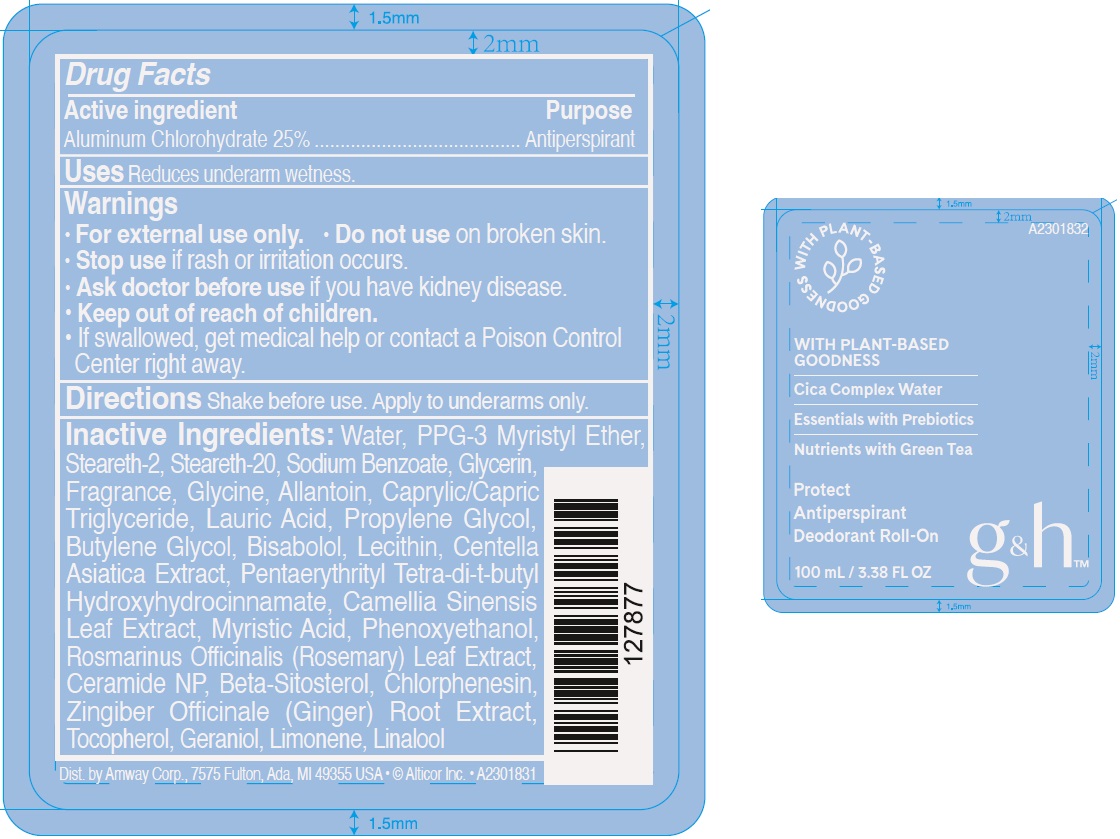 DRUG LABEL: GandH Protect Antiperspirant Deodorant Roll On
NDC: 10056-534 | Form: GEL
Manufacturer: Access Business Group LLC
Category: otc | Type: HUMAN OTC DRUG LABEL
Date: 20241209

ACTIVE INGREDIENTS: ALUMINUM CHLOROHYDRATE 250 mg/1 mL
INACTIVE INGREDIENTS: CHLORPHENESIN; GINGER; TOCOPHEROL; GERANIOL; LIMONENE, (+)-; LINALOOL, (+/-)-; WATER; PPG-3 MYRISTYL ETHER; STEARETH-2; STEARETH-20; SODIUM BENZOATE; GLYCERIN; GLYCINE; ALLANTOIN; MEDIUM-CHAIN TRIGLYCERIDES; LAURIC ACID; PROPYLENE GLYCOL; BUTYLENE GLYCOL; LEVOMENOL; CENTELLA ASIATICA TRITERPENOIDS; PENTAERYTHRITOL TETRAKIS(3-(3,5-DI-TERT-BUTYL-4-HYDROXYPHENYL)PROPIONATE); GREEN TEA LEAF; MYRISTIC ACID; PHENOXYETHANOL; ROSEMARY; CERAMIDE NP; .BETA.-SITOSTEROL

G&H Protect Antiperspirant Deodorant Roll On

Active ingredient

Aluminum Chlorohydrate 25%

Purpose

Antiperspirant

Uses

Reduces underarm wetness.

Warnings

- For external use only.

Do not use

- on broken skin.

Stop use if

rash or irritation occurs.

Ask doctor before use

- if you have kidney disease.

Keep out of reach of children.

- If swallowed, get medical help or contact a Poison Control Center right away.

Directions

Shake before use. Apply to underarms only.

Inactive Ingredients:

Water, PPG-3 Myristyl Ether, Steareth-2, Steareth-20, Sodium Benzoate, Glycerin, Fragrance, Glycine, Allantoin, Caprylic/Capric Triglyceride, Lauric Acid, Propylene Glycol, Butylene Glycol, Bisabolol, Lecithin, Centella Asiatica Extract, Pentaerythrityl Tetra-di-t-butyl Hydroxyhydrocinnamate, Camellia Sinensis Leaf Extract, Myristic Acid, Phenoxyethanol, Rosmarinus Officinalis (Rosemary) Leaf Extract, Ceramide NP, Beta-Sitosterol, Chlorphenesin, Zingiber Officinale (Ginger) Root Extract, Tocopherol, Geraniol, Limonene, Linalool